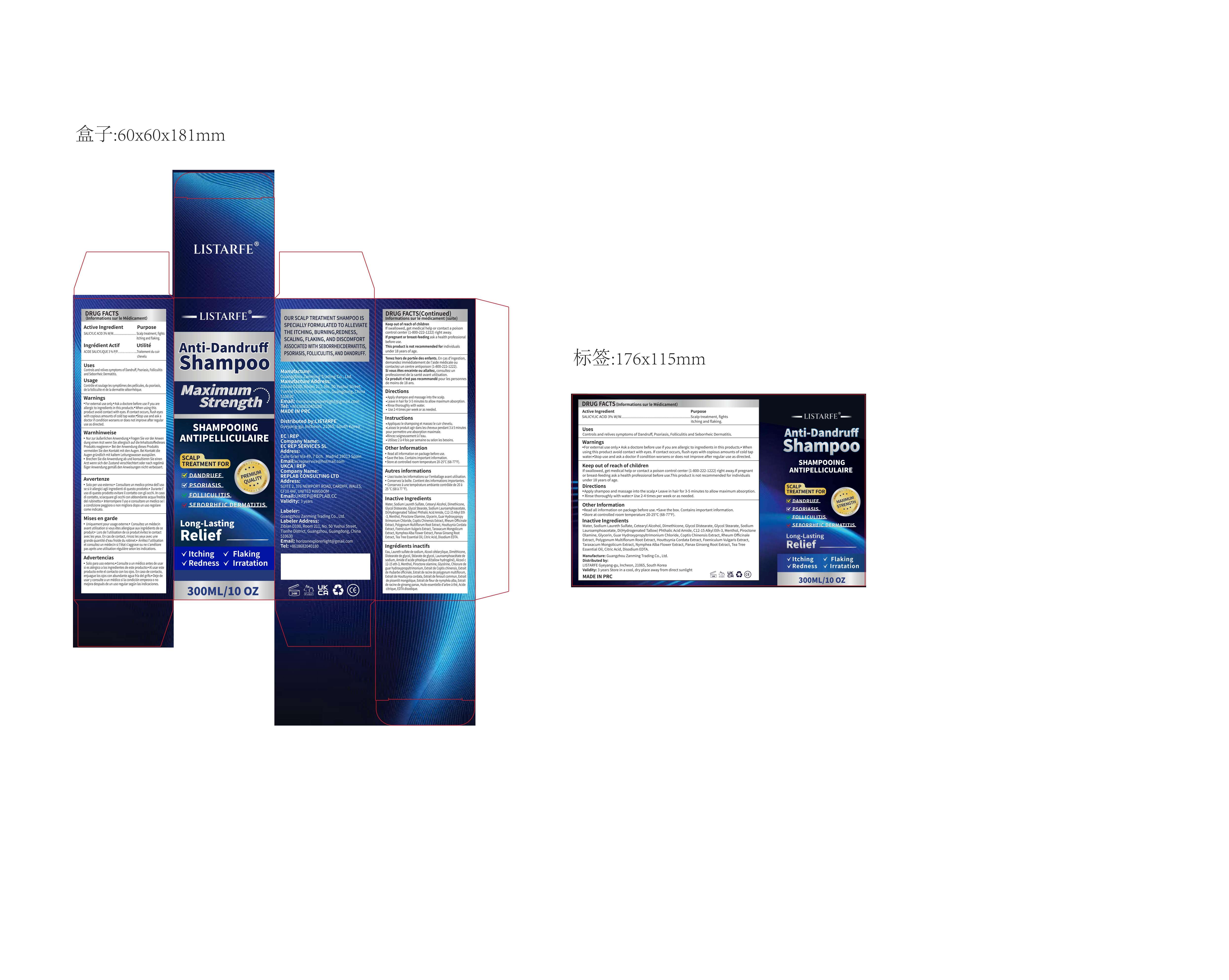 DRUG LABEL: Listarfe Anti-Dandruff Shampoo.
NDC: 85150-005 | Form: SHAMPOO
Manufacturer: Guangzhou Zanming Trading Co., Ltd.
Category: otc | Type: HUMAN OTC DRUG LABEL
Date: 20250328

ACTIVE INGREDIENTS: SALICYLIC ACID 3 g/100 mL
INACTIVE INGREDIENTS: C12-15 ALKYL ETHYLHEXANOATE; PIROCTONE OLAMINE; GLYCOL DISTEARATE; GLYCERIN; EDETATE DISODIUM; COPTIS CHINENSIS WHOLE; RHEUM OFFICINALE WHOLE; WATER; SODIUM LAURETH SULFATE; DIHYDROGENATED TALLOW PHTHALIC ACID AMIDE; MENTHOL; FALLOPIA MULTIFLORA ROOT; HOUTTUYNIA CORDATA FLOWERING TOP; FOENICULUM VULGARE LEAF; ASIAN GINSENG; TEA TREE OIL; CETOSTEARYL ALCOHOL; DIMETHICONE; TARAXACUM MONGOLICUM; SODIUM LAUROAMPHOACETATE; GUAR HYDROXYPROPYLTRIMONIUM CHLORIDE; CITRIC ACID; GLYCOL STEARATE; NYMPHAEA ALBA FLOWER

85150-005

Active Ingredient

SALICYLIC ACID 3% W/W

Purpose

Scalp treatment, fights itching and flaking.

Use

Controls and relives symptoms of Dandruff, Psoriasis, Folliculitis and Seborrheic Dermatitis.

Warnings

■ For external use only.
■ Ask a doctore before use if you are allergic to ingredients in this products.
■ When using this product avoid contact with eyes. If contact occurs, flush eyes with copious amounts of cold tap water.
■ Stop use and ask a doctor if condition worsens or does not improve after regular use as directed.

Do not use

If pregnant or breast-feeding ask a health professional before use.
This product is not recommended for individuals under 18 years of age.

When Using

When using this product avoid contact with eyes. If contact occurs, flush eyes with copious amounts of cold tap water

Stop Use

if condition worsens or does not improve after regular use as directed.

Ask Doctor

If pregnant or breast-feeding ask a health professional before use.

Keep Oot Of Reach Of Children

Keep out of reach of children If swallowed, get medical help or contact a poison control center (1-800-222-1222) right away.

Directions

■ Apply shampoo and massage into the scalp.
■ Leave in hair for 3-5 minutes to allow maximum absorption.
■ Rinse thoroughly with water.
■ Use 2-4 times per week or as needed.

Other information

■Read all information on package before use.
■Save the box. Contains important information.
■Store at controlled room temperature 20-25°C (68-77°F).

Inactive ingredients

Water, Sodium Laureth Sulfate, Cetearyl Alcohol, Dimethicone, Glycol Distearate, Glycol Stearate, Sodium Lauroamphoacetate, Di(Hydrogenated Tallow) Phthalic Acid Amide, C12-15 Alkyl Eth-3, Menthol, Piroctone Olamine, Glycerin, Guar Hydroxypropyltrimonium Chloride, Coptis Chinensis Extract, Rheum Officinale Extract, Polygonum Multiflorum Root Extract, Houttuynia Cordata Extract, Foeniculum Vulgaris Extract, Taraxacum Mongolicum Extract, Nymphea Alba Flower Extract, Panax Ginseng Root Extract, Tea Tree Essential Oil, Citric Acid, Disodium EDTA.